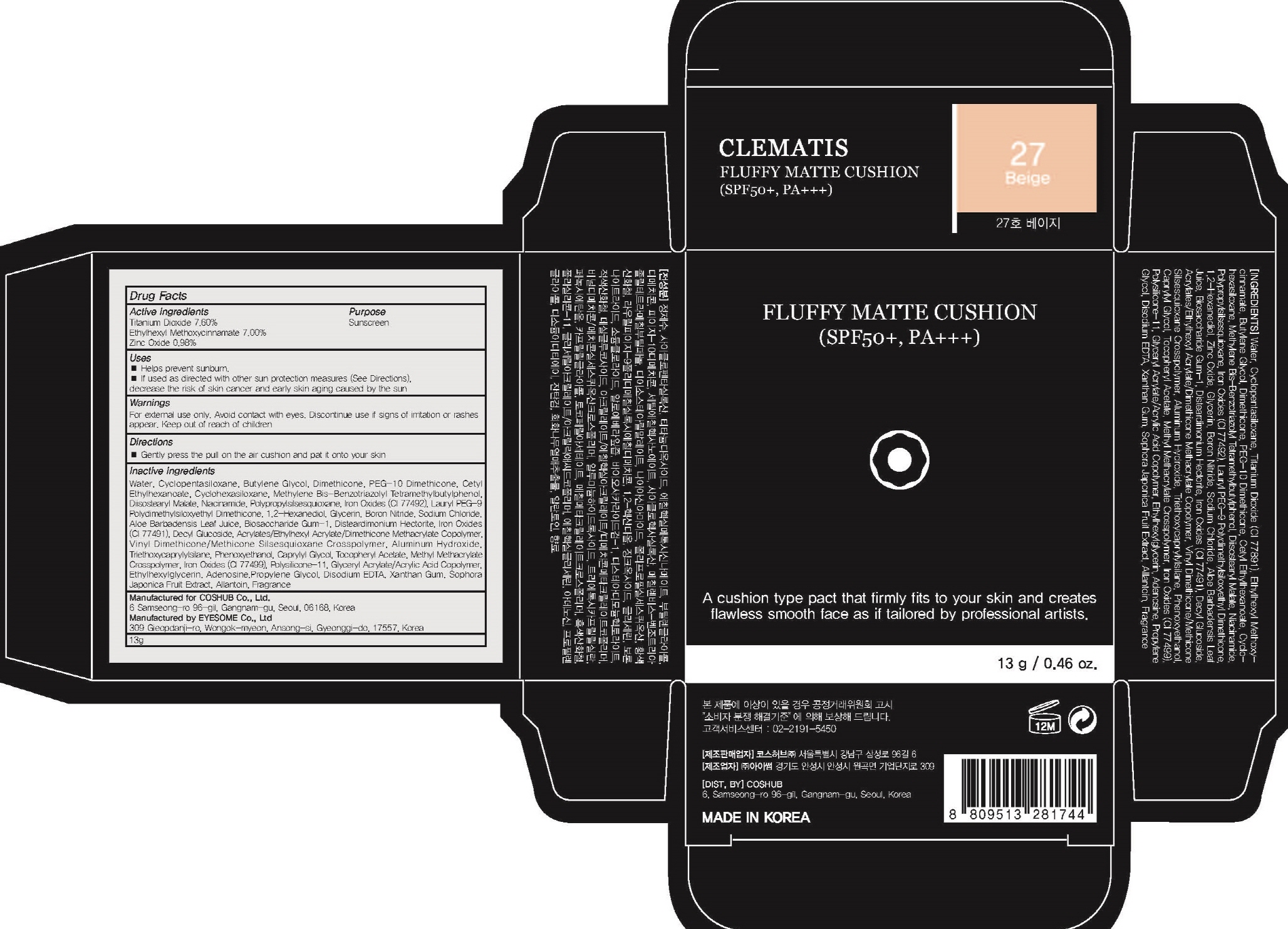 DRUG LABEL: CLEMATIS FLUFFY MATTE CUSHION 27 Beige
NDC: 71702-050 | Form: POWDER
Manufacturer: Coshub Co., Ltd.
Category: otc | Type: HUMAN OTC DRUG LABEL
Date: 20170905

ACTIVE INGREDIENTS: Titanium Dioxide 0.98 g/13 g; Octinoxate 0.91 g/13 g; Zinc Oxide 0.12 g/13 g
INACTIVE INGREDIENTS: Water; Butylene Glycol

ACTIVE INGREDIENT

Active ingredients: Titanium Dioxide 7.60%, Ethylhexyl Methoxycinnamate 7.00%, Zinc Oxide 0.98%

INACTIVE INGREDIENT

Inactive ingredients: Water, Cyclopentasiloxane, Butylene Glycol, Dimethicone, PEG-10 Dimethicone, Cetyl Ethylhexanoate, Cyclohexasiloxane, Methylene Bis-Benzotriazolyl Tetramethylbutylphenol, Diisostearyl Malate, Niacinamide, Polypropylsilsesquioxane, Iron Oxides (CI 77492), Lauryl PEG-9 Polydimethylsiloxyethyl Dimethicone, 1,2-Hexanediol, Glycerin, Boron Nitride, Sodium Chloride, Aloe Barbadensis Leaf Juice, Biosaccharide Gum-1, Disteardimonium Hectorite, Iron Oxides (CI 77491), Decyl Glucoside, Acrylates/Ethylhexyl Acrylate/Dimethicone Methacrylate Copolymer, Vinyl Dimethicone/Methicone Silsesquioxane Crosspolymer, Aluminum Hydroxide, Triethoxycaprylylsilane, Phenoxyethanol, Caprylyl Glycol, Tocopheryl Acetate, Methyl Methacrylate Crosspolymer, Iron Oxides (CI 77499), Polysilicone-11, Glyceryl Acrylate/Acrylic Acid Copolymer, Ethylhexylglycerin, Adenosine,Propylene Glycol, Disodium EDTA, Xanthan Gum, Sophora Japonica Fruit Extract, Allantoin, Fragrance

PURPOSE

Purpose: Sunscreen

WARNINGS

Warnings: For external use only. Avoid contact with eyes. Discontinue use if signs of irritation or rashes appear. Keep out of reach of children.

DESCRIPTION

Uses: - Helps prevent sunburn. - If used as directed with other sun protection measures (See Directions), decrease the risk of skin cancer and early skin aging caused by the sun

Directions: Gently press the pull on the air cushion and pat it onto your skin